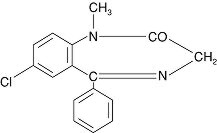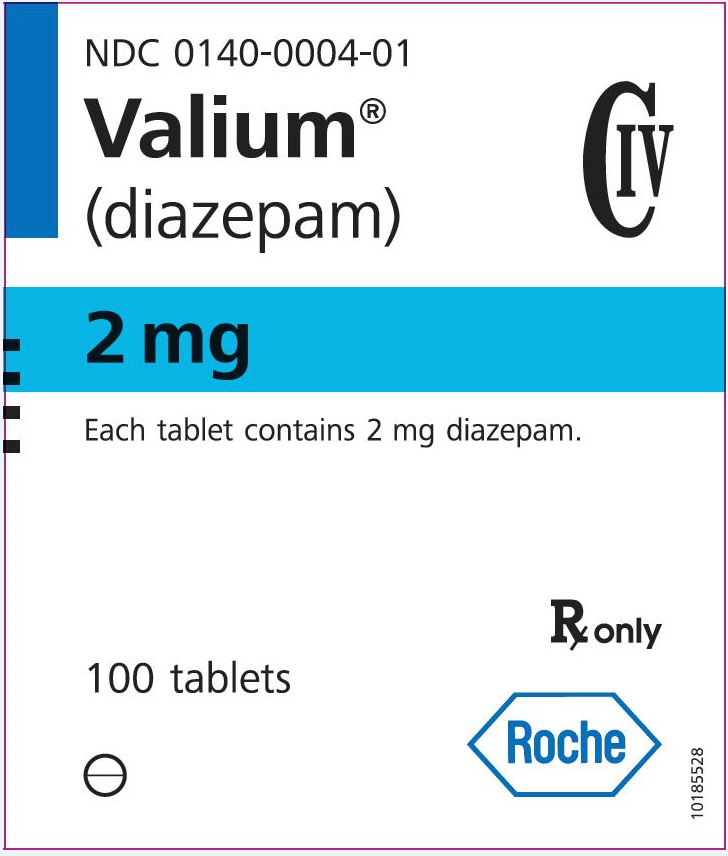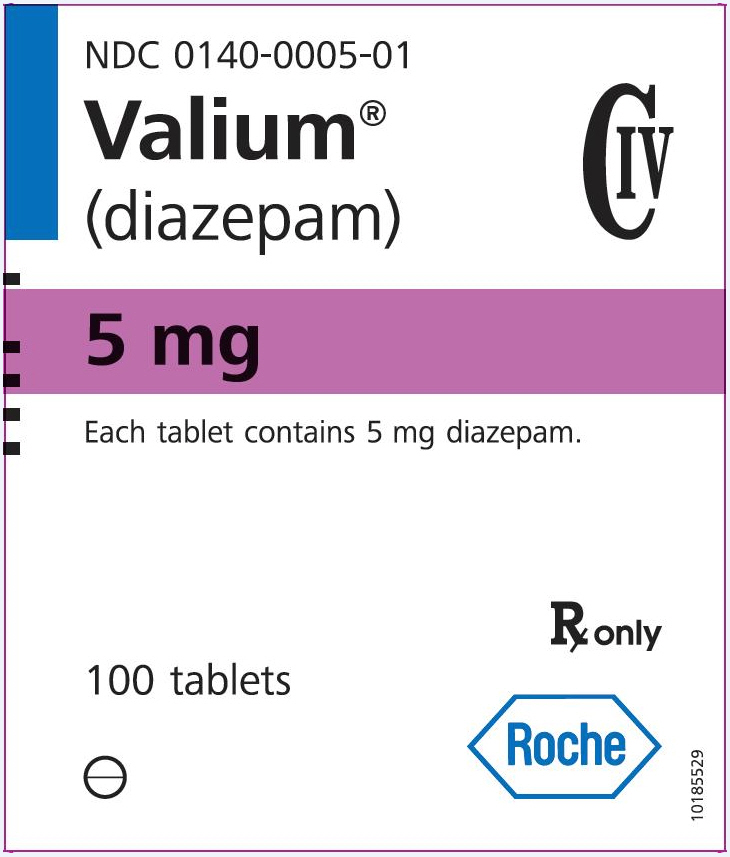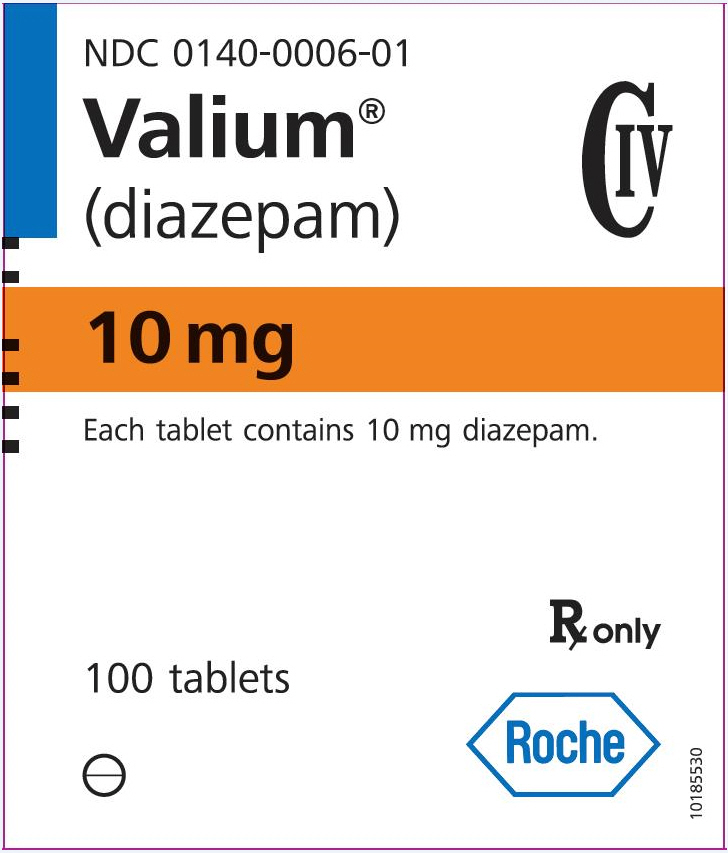 DRUG LABEL: Valium
NDC: 0140-0004 | Form: TABLET
Manufacturer: Roche Laboratories Inc.
Category: prescription | Type: HUMAN PRESCRIPTION DRUG LABEL
Date: 20251201
DEA Schedule: CIV

ACTIVE INGREDIENTS: DIAZEPAM 2 mg/1 1
INACTIVE INGREDIENTS: ANHYDROUS LACTOSE; STARCH, CORN; CALCIUM STEARATE

VALIUM® CIV
brand of diazepam
Tablets

WARNING: RISKS FROM CONCOMITANT USE WITH OPIOIDS; ABUSE, MISUSE, AND ADDICTION; and DEPENDENCE AND WITHDRAWAL REACTIONS

- Concomitant use of benzodiazepines and opioids may result in profound sedation, respiratory depression, coma, and death. Reserve concomitant prescribing of these drugs in patients for whom alternative treatment options are inadequate. Limit dosages and durations to the minimum required. Follow patients for signs and symptoms of respiratory depression and sedation (see WARNINGS and PRECAUTIONS).
- The use of benzodiazepines, including VALIUM, exposes users to risks of abuse, misuse, and addiction, which can lead to overdose or death. Abuse and misuse of benzodiazepines commonly involve concomitant use of other medications, alcohol, and/or illicit substances, which is associated with an increased frequency of serious adverse outcomes. Before prescribing VALIUM and throughout treatment, assess each patient's risk for abuse, misuse, and addiction (see WARNINGS).
- The continued use of benzodiazepines, including VALIUM, may lead to clinically significant physical dependence. The risks of dependence and withdrawal increase with longer treatment duration and higher daily dose. Abrupt discontinuation or rapid dosage reduction of VALIUM after continued use may precipitate acute withdrawal reactions, which can be life-threatening. To reduce the risk of withdrawal reactions, use a gradual taper to discontinue VALIUM or reduce the dosage (see DOSAGE AND ADMINISTRATION and WARNINGS).

DESCRIPTION

Valium (diazepam) is a benzodiazepine derivative. The chemical name of diazepam is 7-chloro-1,3-dihydro-1-methyl-5-phenyl-2H-1,4-benzodiazepin-2-one. It is a colorless to light yellow crystalline compound, insoluble in water. The empirical formula is C16H13ClN2O and the molecular weight is 284.75. The structural formula is as follows:

Valium is available for oral administration as tablets containing 2 mg, 5 mg or 10 mg diazepam. In addition to the active ingredient diazepam, each tablet contains the following inactive ingredients: anhydrous lactose, corn starch, pregelatinized starch and calcium stearate with the following dyes: 5-mg tablets contain FD&C Yellow No. 6 and D&C Yellow No. 10; 10-mg tablets contain FD&C Blue No. 1. Valium 2-mg tablets contain no dye.

CLINICAL PHARMACOLOGY

Diazepam is a benzodiazepine that exerts anxiolytic, sedative, muscle-relaxant, anticonvulsant and amnestic effects. Most of these effects are thought to result from a facilitation of the action of gamma aminobutyric acid (GABA), an inhibitory neurotransmitter in the central nervous system.

Pharmacokinetics

Absorption

After oral administration >90% of diazepam is absorbed and the average time to achieve peak plasma concentrations is 1 – 1.5 hours with a range of 0.25 to 2.5 hours. Absorption is delayed and decreased when administered with a moderate fat meal. In the presence of food mean lag times are approximately 45 minutes as compared with 15 minutes when fasting. There is also an increase in the average time to achieve peak concentrations to about 2.5 hours in the presence of food as compared with 1.25 hours when fasting. This results in an average decrease in Cmax of 20% in addition to a 27% decrease in AUC (range 15% to 50%) when administered with food.

Distribution

Diazepam and its metabolites are highly bound to plasma proteins (diazepam 98%). Diazepam and its metabolites cross the blood-brain and placental barriers and are also found in breast milk in concentrations approximately one tenth of those in maternal plasma (days 3 to 9 post-partum). In young healthy males, the volume of distribution at steady-state is 0.8 to 1.0 L/kg. The decline in the plasma concentration-time profile after oral administration is biphasic. The initial distribution phase has a half-life of approximately 1 hour, although it may range up to >3 hours.

Metabolism

Diazepam is N-demethylated by CYP3A4 and 2C19 to the active metabolite N-desmethyldiazepam, and is hydroxylated by CYP3A4 to the active metabolite temazepam. N-desmethyldiazepam and temazepam are both further metabolized to oxazepam. Temazepam and oxazepam are largely eliminated by glucuronidation.

Elimination

The initial distribution phase is followed by a prolonged terminal elimination phase (half-life up to 48 hours). The terminal elimination half-life of the active metabolite N-desmethyldiazepam is up to 100 hours. Diazepam and its metabolites are excreted mainly in the urine, predominantly as their glucuronide conjugates. The clearance of diazepam is 20 to 30 mL/min in young adults. Diazepam accumulates upon multiple dosing and there is some evidence that the terminal elimination half-life is slightly prolonged.

Pharmacokinetics in Special Populations

Children

In children 3 - 8 years old the mean half-life of diazepam has been reported to be 18 hours.

Newborns

In full term infants, elimination half-lives around 30 hours have been reported, with a longer average half-life of 54 hours reported in premature infants of 28 - 34 weeks gestational age and 8 - 81 days post-partum. In both premature and full term infants the active metabolite desmethyldiazepam shows evidence of continued accumulation compared to children. Longer half-lives in infants may be due to incomplete maturation of metabolic pathways.

Geriatric

Elimination half-life increases by approximately 1 hour for each year of age beginning with a half-life of 20 hours at 20 years of age. This appears to be due to an increase in volume of distribution with age and a decrease in clearance. Consequently, the elderly may have lower peak concentrations, and on multiple dosing higher trough concentrations. It will also take longer to reach steady-state. Conflicting information has been published on changes of plasma protein binding in the elderly. Reported changes in free drug may be due to significant decreases in plasma proteins due to causes other than simply aging.

Hepatic Insufficiency

In mild and moderate cirrhosis, average half-life is increased. The average increase has been variously reported from 2-fold to 5-fold, with individual half-lives over 500 hours reported. There is also an increase in volume of distribution, and average clearance decreases by almost half. Mean half-life is also prolonged with hepatic fibrosis to 90 hours (range 66 - 104 hours), with chronic active hepatitis to 60 hours (range 26 - 76 hours), and with acute viral hepatitis to 74 hours (range 49 - 129). In chronic active hepatitis, clearance is decreased by almost half.

INDICATIONS

Valium is indicated for the management of anxiety disorders or for the short-term relief of the symptoms of anxiety. Anxiety or tension associated with the stress of everyday life usually does not require treatment with an anxiolytic.

In acute alcohol withdrawal, Valium may be useful in the symptomatic relief of acute agitation, tremor, impending or acute delirium tremens and hallucinosis.

Valium is a useful adjunct for the relief of skeletal muscle spasm due to reflex spasm to local pathology (such as inflammation of the muscles or joints, or secondary to trauma), spasticity caused by upper motor neuron disorders (such as cerebral palsy and paraplegia), athetosis, and stiff-man syndrome.

Oral Valium may be used adjunctively in convulsive disorders, although it has not proved useful as the sole therapy.

The effectiveness of Valium in long-term use, that is, more than 4 months, has not been assessed by systematic clinical studies. The physician should periodically reassess the usefulness of the drug for the individual patient.

CONTRAINDICATIONS

Valium is contraindicated in patients with a known hypersensitivity to diazepam and, because of lack of sufficient clinical experience, in pediatric patients under 6 months of age. Valium is also contraindicated in patients with myasthenia gravis, severe respiratory insufficiency, severe hepatic insufficiency, and sleep apnea syndrome. It may be used in patients with open-angle glaucoma who are receiving appropriate therapy, but is contraindicated in acute narrow-angle glaucoma.

WARNINGS

Risks from Concomitant Use with Opioids

Concomitant use of benzodiazepines, including Valium, and opioids may result in profound sedation, respiratory depression, coma, and death. Because of these risks, reserve concomitant prescribing of these drugs in patients for whom alternative treatment options are inadequate.

Observational studies have demonstrated that concomitant use of opioid analgesics and benzodiazepines increases the risk of drug-related mortality compared to use of opioids alone. If a decision is made to prescribe Valium concomitantly with opioids, prescribe the lowest effective dosages and minimum durations of concomitant use, and follow patients closely for signs and symptoms of respiratory depression and sedation. In patients already receiving an opioid analgesic, prescribe a lower initial dose of Valium than indicated in the absence of an opioid and titrate based on clinical response. If an opioid is initiated in a patient already taking Valium, prescribe a lower initial dose of the opioid and titrate based upon clinical response.

Advise both patients and caregivers about the risks of respiratory depression and sedation when Valium is used with opioids. Advise patients not to drive or operate heavy machinery until the effects of concomitant use with the opioid have been determined (see PRECAUTIONS: Drug Interactions).

Abuse, Misuse, and Addiction

The use of benzodiazepines, including Valium, exposes users to the risks of abuse, misuse, and addiction, which can lead to overdose or death. Abuse and misuse of benzodiazepines often (but not always) involve the use of doses greater than the maximum recommended dosage and commonly involve concomitant use of other medications, alcohol, and/or illicit substances, which is associated with an increased frequency of serious adverse outcomes, including respiratory depression, overdose, or death (see DRUG ABUSE AND DEPENDENCE: Abuse).

Before prescribing Valium and throughout treatment, assess each patient's risk for abuse, misuse, and addiction (e.g., using a standardized screening tool). Use of Valium, particularly in patients at elevated risk, necessitates counseling about the risks and proper use of Valium along with monitoring for signs and symptoms of abuse, misuse, and addiction. Prescribe the lowest effective dosage; avoid or minimize concomitant use of CNS depressants and other substances associated with abuse, misuse, and addiction (e.g., opioid analgesics, stimulants); and advise patients on the proper disposal of unused drug. If a substance use disorder is suspected, evaluate the patient and institute (or refer them for) early treatment, as appropriate.

Dependence and Withdrawal Reactions

To reduce the risk of withdrawal reactions, use a gradual taper to discontinue Valium or reduce the dosage (a patient-specific plan should be used to taper the dose) (see DOSAGE AND ADMINISTRATION: Discontinuation or Dosage Reduction of Valium).

Patients at an increased risk of withdrawal adverse reactions after benzodiazepine discontinuation or rapid dosage reduction include those who take higher dosages, and those who have had longer durations of use.

Acute Withdrawal Reactions

The continued use of benzodiazepines, including Valium, may lead to clinically significant physical dependence. Abrupt discontinuation or rapid dosage reduction of Valium after continued use, or administration of flumazenil (a benzodiazepine antagonist) may precipitate acute withdrawal reactions, which can be life-threatening (e.g., seizures) (see DRUG ABUSE AND DEPENDENCE: Dependence).

Protracted Withdrawal Syndrome

In some cases, benzodiazepine users have developed a protracted withdrawal syndrome with withdrawal symptoms lasting weeks to more than 12 months (see DRUG ABUSE AND DEPENDENCE: Dependence).

Valium is not recommended in the treatment of psychotic patients and should not be employed instead of appropriate treatment.

Since Valium has a central nervous system depressant effect, patients should be advised against the simultaneous ingestion of alcohol and other CNS-depressant drugs during Valium therapy.

As with other agents that have anticonvulsant activity, when Valium is used as an adjunct in treating convulsive disorders, the possibility of an increase in the frequency and/or severity of grand mal seizures may require an increase in the dosage of standard anticonvulsant medication. Abrupt withdrawal of Valium in such cases may also be associated with a temporary increase in the frequency and/or severity of seizures.

Pregnancy

An increased risk of congenital malformations and other developmental abnormalities associated with the use of benzodiazepine drugs during pregnancy has been suggested. There may also be non-teratogenic risks associated with the use of benzodiazepines during pregnancy. There have been reports of neonatal flaccidity, respiratory and feeding difficulties, and hypothermia in children born to mothers who have been receiving benzodiazepines late in pregnancy. In addition, children born to mothers receiving benzodiazepines on a regular basis late in pregnancy may be at some risk of experiencing withdrawal symptoms during the postnatal period.

Diazepam has been shown to be teratogenic in mice and hamsters when given orally at daily doses of 100 mg/kg or greater (approximately eight times the maximum recommended human dose [MRHD=1 mg/kg/day] or greater on a mg/m^2 basis). Cleft palate and encephalopathy are the most common and consistently reported malformations produced in these species by administration of high, maternally toxic doses of diazepam during organogenesis. Rodent studies have indicated that prenatal exposure to diazepam doses similar to those used clinically can produce long-term changes in cellular immune responses, brain neurochemistry, and behavior.

In general, the use of diazepam in women of childbearing potential, and more specifically during known pregnancy, should be considered only when the clinical situation warrants the risk to the fetus. The possibility that a woman of childbearing potential may be pregnant at the time of institution of therapy should be considered. If this drug is used during pregnancy, or if the patient becomes pregnant while taking this drug, the patient should be apprised of the potential hazard to the fetus. Patients should also be advised that if they become pregnant during therapy or intend to become pregnant they should communicate with their physician about the desirability of discontinuing the drug.

Labor and Delivery

Special care must be taken when Valium is used during labor and delivery, as high single doses may produce irregularities in the fetal heart rate and hypotonia, poor sucking, hypothermia, and moderate respiratory depression in the neonates. With newborn infants it must be remembered that the enzyme system involved in the breakdown of the drug is not yet fully developed (especially in premature infants).

Nursing Mothers

Diazepam passes into breast milk. Breastfeeding is therefore not recommended in patients receiving Valium.

PRECAUTIONS

General

If Valium is to be combined with other psychotropic agents or anticonvulsant drugs, careful consideration should be given to the pharmacology of the agents to be employed - particularly with known compounds that may potentiate the action of diazepam, such as phenothiazines, narcotics, barbiturates, MAO inhibitors and other antidepressants (see Drug Interactions).

The usual precautions are indicated for severely depressed patients or those in whom there is any evidence of latent depression or anxiety associated with depression, particularly the recognition that suicidal tendencies may be present and protective measures may be necessary.

Psychiatric and paradoxical reactions are known to occur when using benzodiazepines (see ADVERSE REACTIONS). Should this occur, use of the drug should be discontinued. These reactions are more likely to occur in children and the elderly.

A lower dose is recommended for patients with chronic respiratory insufficiency, due to the risk of respiratory depression.

Benzodiazepines should be used with extreme caution in patients with a history of alcohol or drug abuse (see DRUG ABUSE AND DEPENDENCE).

In debilitated patients, it is recommended that the dosage be limited to the smallest effective amount to preclude the development of ataxia or oversedation (2 mg to 2.5 mg once or twice daily, initially, to be increased gradually as needed and tolerated).

Some loss of response to the effects of benzodiazepines may develop after repeated use of Valium for a prolonged time.

Information for Patients

Advise the patient to read the FDA-approved patient labeling (Medication Guide).

Risks from Concomitant Use with Opioids

Advise both patients and caregivers about the risks of potentially fatal respiratory depression and sedation when Valium is used with opioids and not to use such drugs concomitantly unless supervised by a health care provider. Advise patients not to drive or operate heavy machinery until the effects of concomitant use with the opioid have been determined (see WARNINGS: Risks from Concomitant Use with Opioids and PRECAUTIONS: Drug Interactions).

Abuse, Misuse, and Addiction

Inform patients that the use of Valium, even at recommended dosages, exposes users to risks of abuse, misuse, and addiction, which can lead to overdose and death, especially when used in combination with other medications (e.g., opioid analgesics), alcohol, and/or illicit substances. Inform patients about the signs and symptoms of benzodiazepine abuse, misuse, and addiction; to seek medical help if they develop these signs and/or symptoms; and on the proper disposal of unused drug (see WARNINGS: Abuse, Misuse, and Addiction and DRUG ABUSE AND DEPENDENCE).

Withdrawal Reactions

Inform patients that the continued use of Valium may lead to clinically significant physical dependence and that abrupt discontinuation or rapid dosage reduction of Valium may precipitate acute withdrawal reactions, which can be life-threatening. Inform patients that in some cases, patients taking benzodiazepines have developed a protracted withdrawal syndrome with withdrawal symptoms lasting weeks to more than 12 months. Instruct patients that discontinuation or dosage reduction of Valium may require a slow taper (see WARNINGS: Dependence and Withdrawal Reactions and DRUG ABUSE AND DEPENDENCE).

Patients should be advised against the simultaneous ingestion of alcohol and other CNS-depressant drugs during Valium therapy. As is true of most CNS-acting drugs, patients receiving Valium should be cautioned against engaging in hazardous occupations requiring complete mental alertness, such as operating machinery or driving a motor vehicle.

Drug Interactions

Opioids

The concomitant use of benzodiazepines and opioids increases the risk of respiratory depression because of actions at different receptor sites in the CNS that control respiration. Benzodiazepines interact at GABAA sites and opioids interact primarily at mu receptors. When benzodiazepines and opioids are combined, the potential for benzodiazepines to significantly worsen opioid-related respiratory depression exists. Limit dosage and duration of concomitant use of benzodiazepines and opioids, and monitor patients closely for respiratory depression and sedation.

Centrally Acting Agents

If Valium is to be combined with other centrally acting agents, careful consideration should be given to the pharmacology of the agents employed particularly with compounds that may potentiate or be potentiated by the action of Valium, such as phenothiazines, antipsychotics, anxiolytics/sedatives, hypnotics, anticonvulsants, narcotic analgesics, anesthetics, sedative antihistamines, narcotics, barbiturates, MAO inhibitors and other antidepressants.

Alcohol

Concomitant use with alcohol is not recommended due to enhancement of the sedative effect.

Antacids

Diazepam peak concentrations are 30% lower when antacids are administered concurrently. However, there is no effect on the extent of absorption. The lower peak concentrations appear due to a slower rate of absorption, with the time required to achieve peak concentrations on average 20 - 25 minutes greater in the presence of antacids. However, this difference was not statistically significant.

Compounds Which Inhibit Certain Hepatic Enzymes

There is a potentially relevant interaction between diazepam and compounds which inhibit certain hepatic enzymes (particularly cytochrome P450 3A and 2C19). Data indicate that these compounds influence the pharmacokinetics of diazepam and may lead to increased and prolonged sedation. At present, this reaction is known to occur with cimetidine, ketoconazole, fluvoxamine, fluoxetine, and omeprazole.

Phenytoin

There have also been reports that the metabolic elimination of phenytoin is decreased by diazepam.

Carcinogenesis, Mutagenesis, Impairment of Fertility

In studies in which mice and rats were administered diazepam in the diet at a dose of 75 mg/kg/day (approximately 6 and 12 times, respectively, the maximum recommended human dose [MRHD=1 mg/kg/day] on a mg/m^2 basis) for 80 and 104 weeks, respectively, an increased incidence of liver tumors was observed in males of both species. The data currently available are inadequate to determine the mutagenic potential of diazepam. Reproduction studies in rats showed decreases in the number of pregnancies and in the number of surviving offspring following administration of an oral dose of 100 mg/kg/day (approximately 16 times the MRHD on a mg/m^2 basis) prior to and during mating and throughout gestation and lactation. No adverse effects on fertility or offspring viability were noted at a dose of 80 mg/kg/day (approximately 13 times the MRHD on a mg/m^2 basis).

Pregnancy

Category D

(see WARNINGS: Pregnancy).

Pediatric Use

Safety and effectiveness in pediatric patients below the age of 6 months have not been established.

Geriatric Use

In elderly patients, it is recommended that the dosage be limited to the smallest effective amount to preclude the development of ataxia or oversedation (2 mg to 2.5 mg once or twice daily, initially to be increased gradually as needed and tolerated).

Extensive accumulation of diazepam and its major metabolite, desmethyldiazepam, has been noted following chronic administration of diazepam in healthy elderly male subjects. Metabolites of this drug are known to be substantially excreted by the kidney, and the risk of toxic reactions may be greater in patients with impaired renal function. Because elderly patients are more likely to have decreased renal function, care should be taken in dose selection, and it may be useful to monitor renal function.

Hepatic Insufficiency

Decreases in clearance and protein binding, and increases in volume of distribution and half-life have been reported in patients with cirrhosis. In such patients, a 2- to 5- fold increase in mean half-life has been reported. Delayed elimination has also been reported for the active metabolite desmethyldiazepam. Benzodiazepines are commonly implicated in hepatic encephalopathy. Increases in half-life have also been reported in hepatic fibrosis and in both acute and chronic hepatitis (see CLINICAL PHARMACOLOGY: Pharmacokinetics in Special Populations: Hepatic Insufficiency).

ADVERSE REACTIONS

Side effects most commonly reported were drowsiness, fatigue, muscle weakness, and ataxia. The following have also been reported:

Central Nervous System: confusion, depression, dysarthria, headache, slurred speech, tremor, vertigo

Gastrointestinal System: constipation, nausea, gastrointestinal disturbances

Special Senses: blurred vision, diplopia, dizziness

Cardiovascular System: hypotension

Psychiatric and Paradoxical Reactions: stimulation, restlessness, acute hyperexcited states, anxiety, agitation, aggressiveness, irritability, rage, hallucinations, psychoses, delusions, increased muscle spasticity, insomnia, sleep disturbances, and nightmares. Inappropriate behavior and other adverse behavioral effects have been reported when using benzodiazepines. Should these occur, use of the drug should be discontinued. They are more likely to occur in children and in the elderly.

Urogenital System: incontinence, changes in libido, urinary retention

Skin and Appendages: skin reactions

Laboratories: elevated transaminases and alkaline phosphatase

Other: changes in salivation, including dry mouth, hypersalivation

Antegrade amnesia may occur using therapeutic dosages, the risk increasing at higher dosages. Amnestic effects may be associated with inappropriate behavior.

Minor changes in EEG patterns, usually low-voltage fast activity, have been observed in patients during and after Valium therapy and are of no known significance.

Because of isolated reports of neutropenia and jaundice, periodic blood counts and liver function tests are advisable during long-term therapy.

Postmarketing Experience

Injury, Poisoning and Procedural Complications

There have been reports of falls and fractures in benzodiazepine users. The risk is increased in those taking concomitant sedatives (including alcohol), and in the elderly.

DRUG ABUSE AND DEPENDENCE

Controlled Substance

Valium contains diazepam, a Schedule IV controlled substance.

Abuse

Valium is a benzodiazepine and a CNS depressant with a potential for abuse and addiction. Abuse is the intentional, non-therapeutic use of a drug, even once, for its desirable psychological or physiological effects. Misuse is the intentional use, for therapeutic purposes, of a drug by an individual in a way other than prescribed by a health care provider or for whom it was not prescribed. Drug addiction is a cluster of behavioral, cognitive, and physiological phenomena that may include a strong desire to take the drug, difficulties in controlling drug use (e.g., continuing drug use despite harmful consequences, giving a higher priority to drug use than other activities and obligations), and possible tolerance or physical dependence. Even taking benzodiazepines as prescribed may put patients at risk for abuse and misuse of their medication. Abuse and misuse of benzodiazepines may lead to addiction.

Abuse and misuse of benzodiazepines often (but not always) involve the use of doses greater than the maximum recommended dosage and commonly involve concomitant use of other medications, alcohol, and/or illicit substances, which is associated with an increased frequency of serious adverse outcomes, including respiratory depression, overdose, or death. Benzodiazepines are often sought by individuals who abuse drugs and other substances, and by individuals with addictive disorders (see WARNINGS: Abuse, Misuse, and Addiction).

The following adverse reactions have occurred with benzodiazepine abuse and/or misuse: abdominal pain, amnesia, anorexia, anxiety, aggression, ataxia, blurred vision, confusion, depression, disinhibition, disorientation, dizziness, euphoria, impaired concentration and memory, indigestion, irritability, muscle pain, slurred speech, tremors, and vertigo.

The following severe adverse reactions have occurred with benzodiazepine abuse and/or misuse: delirium, paranoia, suicidal ideation and behavior, seizures, coma, breathing difficulty, and death. Death is more often associated with polysubstance use (especially benzodiazepines with other CNS depressants such as opioids and alcohol).

Dependence

Physical Dependence

Valium may produce physical dependence from continued therapy. Physical dependence is a state that develops as a result of physiological adaptation in response to repeated drug use, manifested by withdrawal signs and symptoms after abrupt discontinuation or a significant dose reduction of a drug. Abrupt discontinuation or rapid dosage reduction of benzodiazepines or administration of flumazenil, a benzodiazepine antagonist, may precipitate acute withdrawal reactions, including seizures, which can be life-threatening. Patients at an increased risk of withdrawal adverse reactions after benzodiazepine discontinuation or rapid dosage reduction include those who take higher dosages (i.e., higher and/or more frequent doses), those who have had longer durations of use (see WARNINGS: Dependence and Withdrawal Reactions).

To reduce the risk of withdrawal reactions, use a gradual taper to discontinue Valium or reduce the dosage (see DOSAGE and ADMINISTRATION: Discontinuation or Dosage Reduction of Valium and WARNINGS: Dependence and Withdrawal Reactions).

Acute withdrawal signs and symptoms associated with benzodiazepines have included abnormal involuntary movements, anxiety, blurred vision, depersonalization, depression, derealization, dizziness, fatigue, gastrointestinal adverse reactions (e.g., nausea, vomiting, diarrhea, weight loss, decreased appetite), headache, hyperacusis, hypertension, irritability, insomnia, memory impairment, muscle pain and stiffness, panic attacks, photophobia, restlessness, tachycardia, and tremor. More severe acute withdrawal signs and symptoms, including life-threatening reactions, have included catatonia, convulsions, delirium tremens, depression, hallucinations, mania, psychosis, seizures, and suicidality.

Protracted withdrawal syndrome associated with benzodiazepines is characterized by anxiety, cognitive impairment, depression, insomnia, formication, motor symptoms (e.g., weakness, tremor, muscle twitches), paresthesia, and tinnitus that persists beyond 4 to 6 weeks after initial benzodiazepine withdrawal. Protracted withdrawal symptoms may last weeks to more than 12 months. As a result, there may be difficulty in differentiating withdrawal symptoms from potential re-emergence or continuation of symptoms for which the benzodiazepine was being used.

Tolerance

Tolerance to Valium may develop from continued therapy. Tolerance is a physiological state characterized by a reduced response to a drug after repeated administration (i.e., a higher dose of a drug is required to produce the same effect that was once obtained at a lower dose). Tolerance to the therapeutic effect of Valium may develop; however, little tolerance develops to the amnestic reactions and other cognitive impairments caused by benzodiazepines.

OVERDOSAGE

Overdose of benzodiazepines is usually manifested by central nervous system depression ranging from drowsiness to coma. In mild cases, symptoms include drowsiness, confusion, and lethargy. In more serious cases, symptoms may include ataxia, diminished reflexes, hypotonia, hypotension, respiratory depression, coma (rarely), and death (very rarely). Overdose of benzodiazepines in combination with other CNS depressants (including alcohol) may be fatal and should be closely monitored.

Management of Overdosage

Following overdose with oral benzodiazepines, general supportive measures should be employed including the monitoring of respiration, pulse, and blood pressure. Vomiting should be induced (within 1 hour) if the patient is conscious. Gastric lavage should be undertaken with the airway protected if the patient is unconscious. Intravenous fluids should be administered. If there is no advantage in emptying the stomach, activated charcoal should be given to reduce absorption. Special attention should be paid to respiratory and cardiac function in intensive care. General supportive measures should be employed, along with intravenous fluids, and an adequate airway maintained. Should hypotension develop, treatment may include intravenous fluid therapy, repositioning, judicious use of vasopressors appropriate to the clinical situation, if indicated, and other appropriate countermeasures. Dialysis is of limited value.

As with the management of intentional overdosage with any drug, it should be considered that multiple agents may have been ingested.

Flumazenil, a specific benzodiazepine-receptor antagonist, is indicated for the complete or partial reversal of the sedative effects of benzodiazepines and may be used in situations when an overdose with a benzodiazepine is known or suspected. Prior to the administration of flumazenil, necessary measures should be instituted to secure airway, ventilation and intravenous access. Flumazenil is intended as an adjunct to, not as a substitute for, proper management of benzodiazepine overdose. Patients treated with flumazenil should be monitored for resedation, respiratory depression and other residual benzodiazepine effects for an appropriate period after treatment. The prescriber should be aware of a risk of seizure in association with flumazenil treatment, particularly in long-term benzodiazepine users and in cyclic antidepressant overdose. Caution should be observed in the use of flumazenil in epileptic patients treated with benzodiazepines. The complete flumazenil package insert, including CONTRAINDICATIONS, WARNINGS, and PRECAUTIONS, should be consulted prior to use.

Withdrawal symptoms of the barbiturate type have occurred after the discontinuation of benzodiazepines (see DRUG ABUSE AND DEPENDENCE).

DOSAGE AND ADMINISTRATION

Dosage should be individualized for maximum beneficial effect. While the usual daily dosages given below will meet the needs of most patients, there will be some who may require higher doses. In such cases dosage should be increased cautiously to avoid adverse effects.

ADULTS: | USUAL DAILY DOSE:
Management of Anxiety Disorders and Relief of Symptoms of Anxiety. | Depending upon severity of symptoms—2 mg to 10 mg, 2 to 4 times daily
Symptomatic Relief in Acute Alcohol Withdrawal. | 10 mg, 3 or 4 times during the first 24 hours, reducing to 5 mg, 3 or 4 times daily as needed
Adjunctively for Relief of Skeletal Muscle Spasm. | 2 mg to 10 mg, 3 or 4 times daily
Adjunctively in Convulsive Disorders. | 2 mg to 10 mg, 2 to 4 times daily
Geriatric Patients, or in the presence of debilitating disease. | 2 mg to 2.5 mg, 1 or 2 times daily initially; increase gradually as needed and tolerated
PEDIATRIC PATIENTS:
Because of varied responses to CNS-acting drugs, initiate therapy with lowest dose and increase as required. Not for use in pediatric patients under 6 months. | 1 mg to 2.5 mg, 3 or 4 times daily initially; increase gradually as needed and tolerated

Discontinuation or Dosage Reduction of Valium

To reduce the risk of withdrawal reactions, use a gradual taper to discontinue Valium or reduce the dosage. If a patient develops withdrawal reactions, consider pausing the taper or increasing the dosage to the previous tapered dosage level. Subsequently decrease the dosage more slowly (see WARNINGS: Dependence and Withdrawal Reactions and DRUG ABUSE AND DEPENDENCE: Dependence).

HOW SUPPLIED

For oral administration, Valium is supplied as round, flat-faced scored tablets with V-shaped perforation and beveled edges. Valium is available as follows: 2 mg, white - bottles of 100 (NDC 0140-0004-01); 5 mg, yellow - bottles of 100 (NDC 0140-0005-01) and 500 (NDC 0140-0005-14); 10 mg, blue - bottles of 100 (NDC 0140-0006-01) and 500 (NDC 0140-0006-14).

Engraved on tablets:

2 mg—2 VALIUM® (front)
ROCHE (twice on scored side)

5 mg—5 VALIUM® (front)
ROCHE (twice on scored side)

10 mg—10 VALIUM® (front)
ROCHE (twice on scored side)

Storage

Store at room temperature 59º to 86ºF (15º to 30ºC). Dispense in tight, light-resistant containers as defined in USP/NF.

VALIUM is a registered trademark of Hoffmann-La Roche, Inc.

Distributed by:

Roche Laboratories Inc. on behalf of Roche Products Inc.
150 Clove Road
Suite 8
Little Falls, NJ 07424

Revised: February 2021

© 2021 Genentech, Inc. All rights reserved.

MEDICATION GUIDE
VALIUM (VAL-ee-um)
(diazepam)
tablets, C-IV

What is the most important information I should know about VALIUM?

- VALIUM is a benzodiazepine medicine. Taking benzodiazepines with opioid medicines, alcohol, or other central nervous system (CNS) depressants (including street drugs) can cause severe drowsiness, breathing problems (respiratory depression), coma and death. Get emergency help right away if any of the following happens:
  - Shallow or slowed breathing,
  - Breathing stops (which may lead to the heart stopping),
  - Excessive sleepiness (sedation).
  Do not drive or operate heavy machinery until you know how taking VALIUM with opioids affects you.
- Risk of abuse, misuse, and addiction. There is a risk of abuse, misuse, and addiction with benzodiazepines, including VALIUM, which can lead to overdose and serious side effects including coma and death.
  - Serious side effects including coma and death have happened in people who have abused or misused benzodiazepines, including VALIUM. These serious side effects may also include delirium, paranoia, suicidal thoughts or actions, seizures, and difficulty breathing. Call your healthcare provider or go to the nearest hospital emergency room right away if you get any of these serious side effects.
  - You can develop an addiction even if you take VALIUM exactly as prescribed by your healthcare provider.
  - Take VALIUM exactly as your healthcare provider prescribed.
  - Do not share your VALIUM with other people.
  - Keep VALIUM in a safe place and away from children.
- Physical dependence and withdrawal reactions. VALIUM can cause physical dependence and withdrawal reactions.
  - Do not suddenly stop taking VALIUM. Stopping VALIUM suddenly can cause serious and life- threatening side effects, including, unusual movements, responses, or expressions, seizures, sudden and severe mental or nervous system changes, depression, seeing or hearing things that others do not see or hear, an extreme increase in activity or talking, losing touch with reality, and suicidal thoughts or actions. Call your healthcare provider or go to the nearest hospital emergency room right away if you get any of these symptoms.
  - Some people who suddenly stop benzodiazepines have symptoms that can last for several weeks to more than 12 months, including, anxiety, trouble remembering, learning, or concentrating, depression, problems sleeping, feeling like insects are crawling under your skin, weakness, shaking, muscle twitching, burning or prickling feeling in your hands, arms, legs or feet, and ringing in your ears.
  - Physical dependence is not the same as drug addiction. Your healthcare provider can tell you more about the differences between physical dependence and drug addiction.
  - Do not take more VALIUM than prescribed or take VALIUM for longer than prescribed.

What is VALIUM?

- VALIUM is a prescription medicine used:
  - to treat anxiety disorders
  - for the short-term relief of the symptoms of anxiety
  - to relieve the symptoms of alcohol withdrawal including agitation, shakiness (tremor), sudden and severe mental or nervous system changes (delirium tremens) and seeing or hearing things that others do not see or hear (hallucinations)
  - along with other medicines for the relief of muscle spasms
  - along with other medicines to treat seizure disorders
- VALIUM is a federal controlled substance (C-IV) because it contains diazepam that can be abused or lead to dependence. Keep VALIUM in a safe place to prevent misuse and abuse. Selling or giving away VALIUM may harm others, and is against the law. Tell your healthcare provider if you have abused or been dependent on alcohol, prescription medicines or street drugs.
- It is not known if VALIUM is safe and effective in children under 6 months of age.
- It is not known if VALIUM is safe and effective for use longer than 4 months.

Do not take VALIUM if you:

- are allergic to diazepam or any of the ingredients in VALIUM. See the end of this Medication Guide for a complete list of ingredients in VALIUM.
- have a disease that can cause muscle weakness called myasthenia gravis
- have severe breathing problems (severe respiratory insufficiency)
- have severe liver problems
- have a sleep problem called sleep apnea syndrome

Before you take VALIUM, tell your healthcare provider about all of your medical conditions, including if you:

- have or have had depression, mood problems, or suicidal thoughts or behavior
- have lung disease or breathing problems
- have liver or kidney problems
- are pregnant or plan to become pregnant. VALIUM may harm your unborn baby. You and your healthcare provider should decide if you should take VALIUM while you are pregnant.
- are breastfeeding or plan to breastfeed. VALIUM passes into your breast milk and may harm your baby. Talk to your healthcare provider about the best way to feed your baby if you take VALIUM. Do not breastfeed while taking VALIUM.

Tell your healthcare provider about all the medicines you take, including prescription and over-the-counter medicines, vitamins, and herbal supplements.
Taking VALIUM with certain other medicines can cause side effects or affect how well VALIUM or the other medicines work. Do not start or stop other medicines without talking to your healthcare provider.

How should I take VALIUM?

- Take VALIUM exactly as your healthcare provider tells you to take it. Your healthcare provider will tell you how much VALIUM to take and when to take it.
- Talk to your healthcare provider about slowly stopping VALIUM to avoid withdrawal symptoms.
- If you take too much VALIUM, call your healthcare provider or go to the nearest hospital emergency room right away.

What are the possible side effects of VALIUM?
VALIUM may cause serious side effects, including:

- See "What is the most important information I should know about VALIUM?"
- Seizures. Taking VALIUM with other medicines used to treat epilepsy can cause an increase in the number or severity of grand mal seizures.
- VALIUM can make you sleepy or dizzy, and can slow your thinking and motor skills.
  - Do not drive, operate heavy machinery, or do other dangerous activities until you know how VALIUM affects you.
  - Do not drink alcohol or take other drugs that may make you sleepy or dizzy while taking VALIUM without first talking to your healthcare provider. When taken with alcohol or drugs that cause sleepiness or dizziness, VALIUM may make your sleepiness or dizziness much worse.
- Like other antiepileptic drugs, VALIUM may cause suicidal thoughts or actions in a very small number of people, about 1 in 500.
  Call your healthcare provider right away if you have any of these symptoms, especially if they are new, worse, or worry you:

- thoughts about suicide or dying
- new or worse depression
- feeling agitated or restless
- trouble sleeping (insomnia)
- acting aggressive, being angry or violent
- other unusual changes in behavior or mood

- attempts to commit suicide
- new or worse anxiety or irritability
- an extreme increase in activity and talking (mania)
- new or worse panic attacks
- acting on dangerous impulses

How can I watch for early symptoms of suicidal thoughts and actions?

- Pay attention to any changes, especially sudden changes, in mood, behaviors, thoughts, or feelings.
- Keep all follow-up visits with your healthcare provider as scheduled.

Call your healthcare provider between visits as needed, especially if you are worried about symptoms. Suicidal thoughts or actions can be caused by things other than medicines. If you have suicidal thoughts or actions, your healthcare provider may check for other causes.
The most common side effects of VALIUM include:

- drowsiness
- muscle weakness
- loss of control of body movements (ataxia)
- fatigue

These are not all the possible side effects of VALIUM. Call your doctor for medical advice about side effects. You may report side effects to FDA at 1-800-FDA-1088.
You may also report side effects to Genentech at 1-888-835-2555.

How should I store VALIUM?

- Store VALIUM in a tightly closed container at room temperature between 68°F to 77°F (20°C to 25°C) and out of the light.
- Keep VALIUM and all medicines out of the reach of children.

General information about the safe and effective use of VALIUM.
Medicines are sometimes prescribed for purposes other than those listed in a Medication Guide. Do not use VALIUM for a condition for which it was not prescribed. Do not give VALIUM to other people, even if they have the same symptoms that you have. It may harm them. You can ask your pharmacist or healthcare provider for information about VALIUM that is written for health professionals.

What are the ingredients in VALIUM?
Active ingredient: diazepam
Inactive ingredients: anhydrous lactose, corn starch, pregelatinized starch and calcium stearate
Distributed by: Roche Laboratories Inc. on behalf of Roche Products Inc.
VALIUM® is a registered trademark of Hoffmann-La Roche, Inc.
For more information, go to www.gene.com/patients/medicines/Valium or call 1-877-436-3683.

This Medication Guide has been approved by the U.S. Food and Drug Administration.

Revised: February/2021

Representative sample of labeling (see the HOW SUPPLIED section for complete listing):

PRINCIPAL DISPLAY PANEL - 2 mg Tablet Bottle Label

NDC 0140-0004-01

Valium®
(diazepam)

CIV

2 mg

Each tablet contains 2 mg diazepam.

Rx only

100 tablets

Roche

10185528

PRINCIPAL DISPLAY PANEL - 5 mg Tablet Bottle Label

NDC 0140-0005-01

Valium®
(diazepam)

CIV

5 mg

Each tablet contains 5 mg diazepam.

Rx only

100 tablets

Roche

10185529

PRINCIPAL DISPLAY PANEL - 10 mg Tablet Bottle Label

NDC 0140-0006-01

Valium®
(diazepam)

CIV

10 mg

Each tablet contains 10 mg diazepam.

Rx only

100 tablets

Roche

10185530